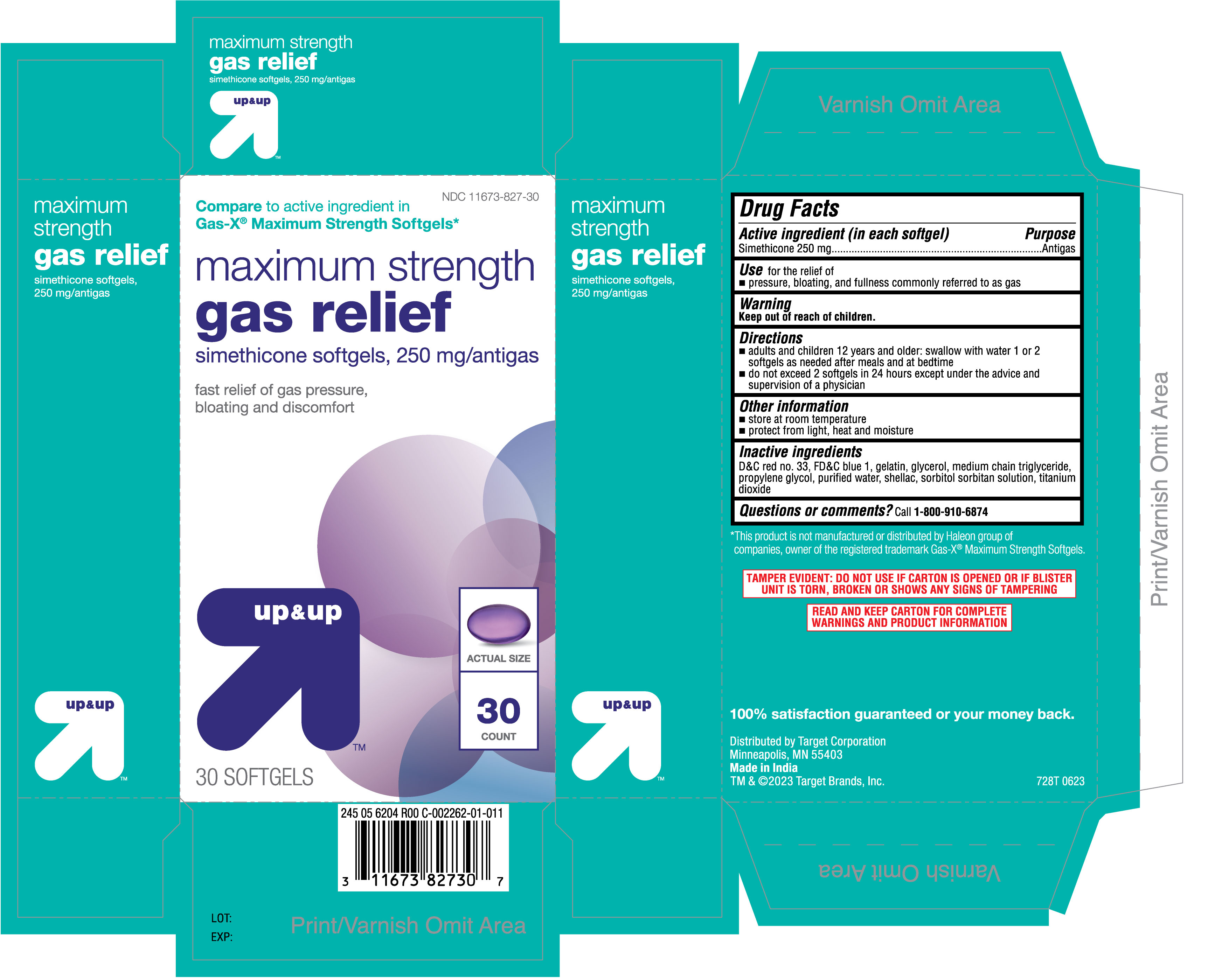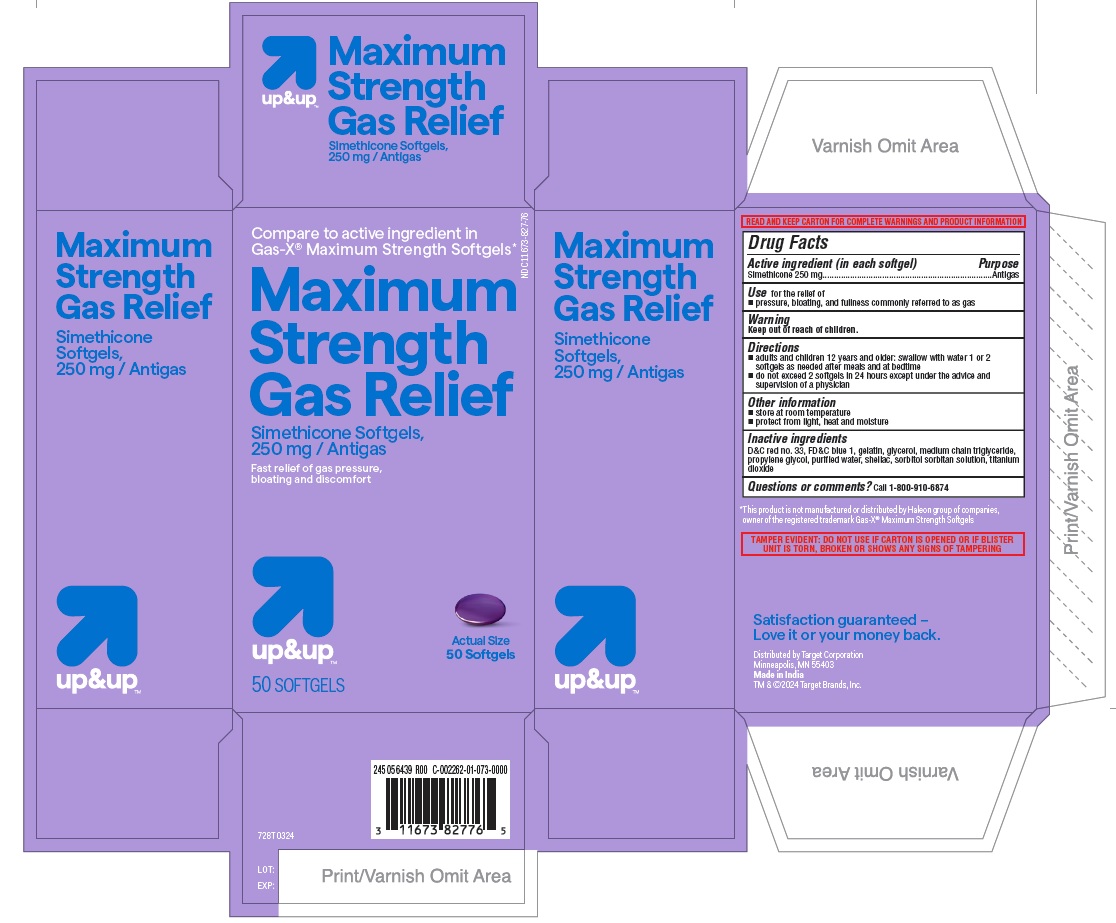 DRUG LABEL: Maximum Strength Gas Relief
NDC: 11673-827 | Form: CAPSULE, LIQUID FILLED
Manufacturer: TARGET CORPORATION
Category: otc | Type: HUMAN OTC DRUG LABEL
Date: 20240513

ACTIVE INGREDIENTS: DIMETHICONE 250 mg/1 1
INACTIVE INGREDIENTS: SORBITAN; TITANIUM DIOXIDE; PROPYLENE GLYCOL; WATER; FD&C BLUE NO. 1; MEDIUM-CHAIN TRIGLYCERIDES; SHELLAC; D&C RED NO. 33; GELATIN; GLYCERIN; SORBITOL

728T Target 11673-827 Simethicone 250 mg Capsules

Active ingredient (in each softgel)

Simethicone 250 mg

Purpose

Antigas

INDICATIONS AND USAGE

Use for the relief of

- pressure, bloating, and fullness commonly referred to as gas

Warning

Keep out of reach of children.

Directions

- adults and children 12 years and older: swallow with water 1 or 2 softgels as needed after meals and at bedtime
- do not exceed 2 softgels in 24 hours except under the advice and supervision of a physician

Other information

- store at room temperature
- protect from light, heat and moisture

Inactive ingredients

D&C red no. 33, FD&C blue 1, gelatin, glycerol, medium chain triglyceride, propylene glycol, purified water, shellac, sorbitol sorbitan solution, titanium dioxide

Questions or comments? Call 1-800-910-6874